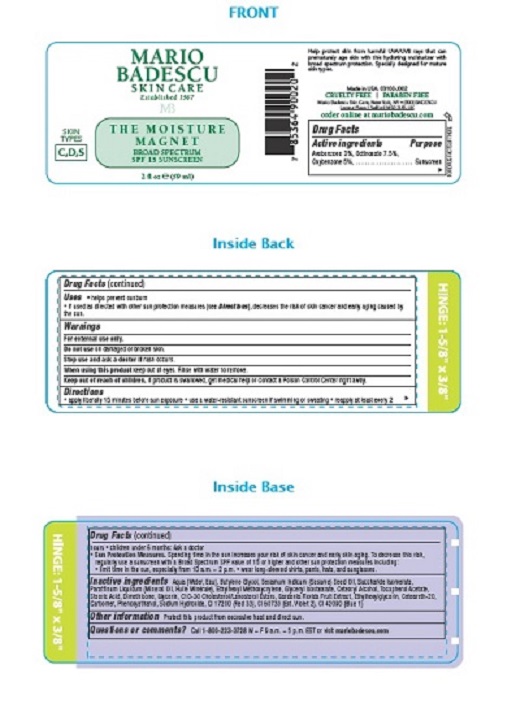 DRUG LABEL: Mario Badescu The Moisture Magnet SPF 15
NDC: 54111-138 | Form: LOTION
Manufacturer: Bentley Laboratories LLC
Category: otc | Type: HUMAN OTC DRUG LABEL
Date: 20240910

ACTIVE INGREDIENTS: AVOBENZONE 1.77 g/59 mL; OCTINOXATE 4.425 g/59 mL; OXYBENZONE 2.95 g/59 mL
INACTIVE INGREDIENTS: WATER; BUTYLENE GLYCOL; SESAME OIL; SACCHARIDE ISOMERATE; MINERAL OIL; ETHYLHEXYL METHOXYCRYLENE; GLYCERYL ISOSTEARATE; CETOSTEARYL ALCOHOL; .ALPHA.-TOCOPHEROL ACETATE; STEARIC ACID; DIMETHICONE; GLYCERIN; C10-30 CHOLESTEROL/LANOSTEROL ESTERS; GARDENIA JASMINOIDES FRUIT; ETHYLHEXYLGLYCERIN; POLYOXYL 20 CETOSTEARYL ETHER; CARBOXYPOLYMETHYLENE; PHENOXYETHANOL; SODIUM HYDROXIDE; D&C RED NO. 33; EXT. D&C VIOLET NO. 2; FD&C BLUE NO. 1

MARIO BADESCU MOISTURE MAGNET SPF 15

DRUG FACTS

Active ingredients

Avobenzone 3%, Octinoxate 7.5%, Oxybenzone 5%

Purpose

Sunscreen

INDICATIONS AND USAGE

Uses • helps prevent sunburn
• If used as directed with other sun protection measures (see Directions), decreases the risk of skin cancer and early aging caused by the sun.

Warnings

For external use only.

Do not use on damaged or broken skin.

Stop use and ask a doctor if rash occurs.

When using this product keep out of eyes. Rinse with water to remove.

Keep out of reach of children. If product is swallowed, get medical help or contact a Poison Control Center right away.

Directions

• apply liberally 15 minutes before sun exposure • use a water-resistant sunscreen if swimming or sweating • reapply at least every 2 hours • children under 6 months: Ask a doctor
• Sun Protection Measures. Spending time in the sun increases your risk of skin cancer and early skin aging. To decrease this risk, regularly use a sunscreen with a Broad Spectrum SPF value of 15 or higher and other sun protection measures including:
• limit time in the sun, especially from 10 a.m. – 2 p.m. • wear long-sleeved shirts, pants, hats, and sunglasses.

INACTIVE INGREDIENT

Inactive ingredients Aqua (Water, Eau), Butylene Glycol, Sesamum Indicum (Sesame) Seed Oil, Saccharide Isomerate, Paraffinum Liquidum (Mineral Oil, Huile Minérale), Ethylhexyl Methoxycrylene, Glyceryl Isostearate, Cetearyl Alcohol, Tocopherol Acetate, Stearic Acid, Dimethicone, Glycerin, C10-30 Cholesterol/Lanosterol Esters, Gardenia Florida Fruit Extract, Ethylhexylglycerin, Ceteareth-20, Carbomer, Phenoxyethanol, Sodium Hydroxide, CI 17200 (Red 33), CI 60730 (Ext. Violet 2), CI 42090 (Blue 1)

Other information Protect this product from excessive heat and direct sun.

Questions or comments? Call 1-800-223-3728 M – F 9 a.m. – 5 p.m. EST or visit mariobadescu.com

Principal Display Panel

MARIO
BADESCU
SKIN CARE
Established 1967
MB

THE MOISTURE
MAGNET
BROAD SPECTRUM
SPF 15 SUNSCREEN

2 fl oz ℮ (59 ml)

SKIN
TYPES
C,D,S

Help protect skin from harmful UVA/UVB rays that can prematurely age skin with this hydrating moisturizer with broad spectrum protection. Specially designed for mature skin types.

Made in USA. 03102-J002
CRUELTY FREE | PARABEN FREE

Mario Badescu Skin Care, New York, NY • (800) BADESCU
Leceur Plaza 1 Salford M50 3UB, UK

order online at mariobadescu.com

res